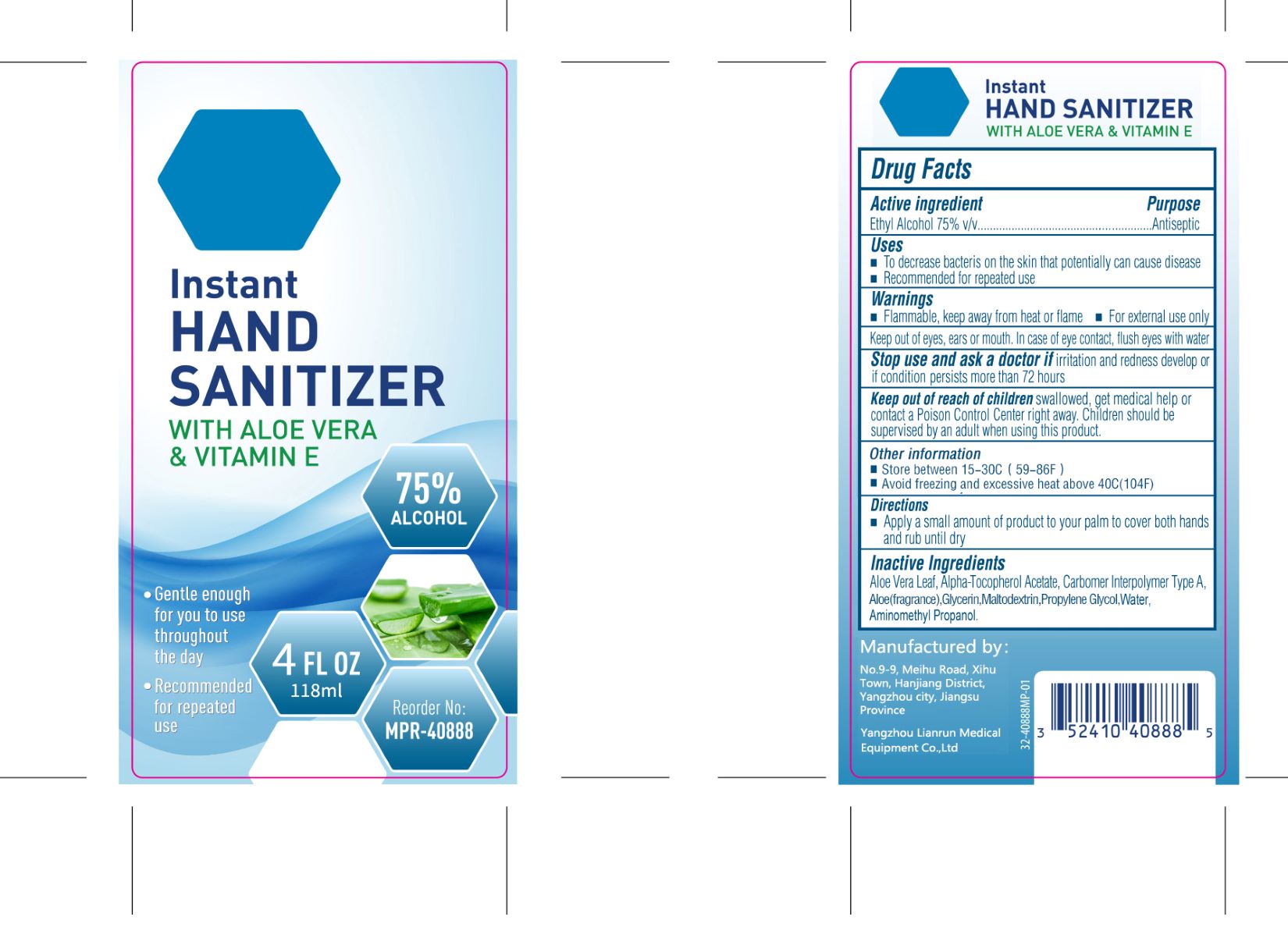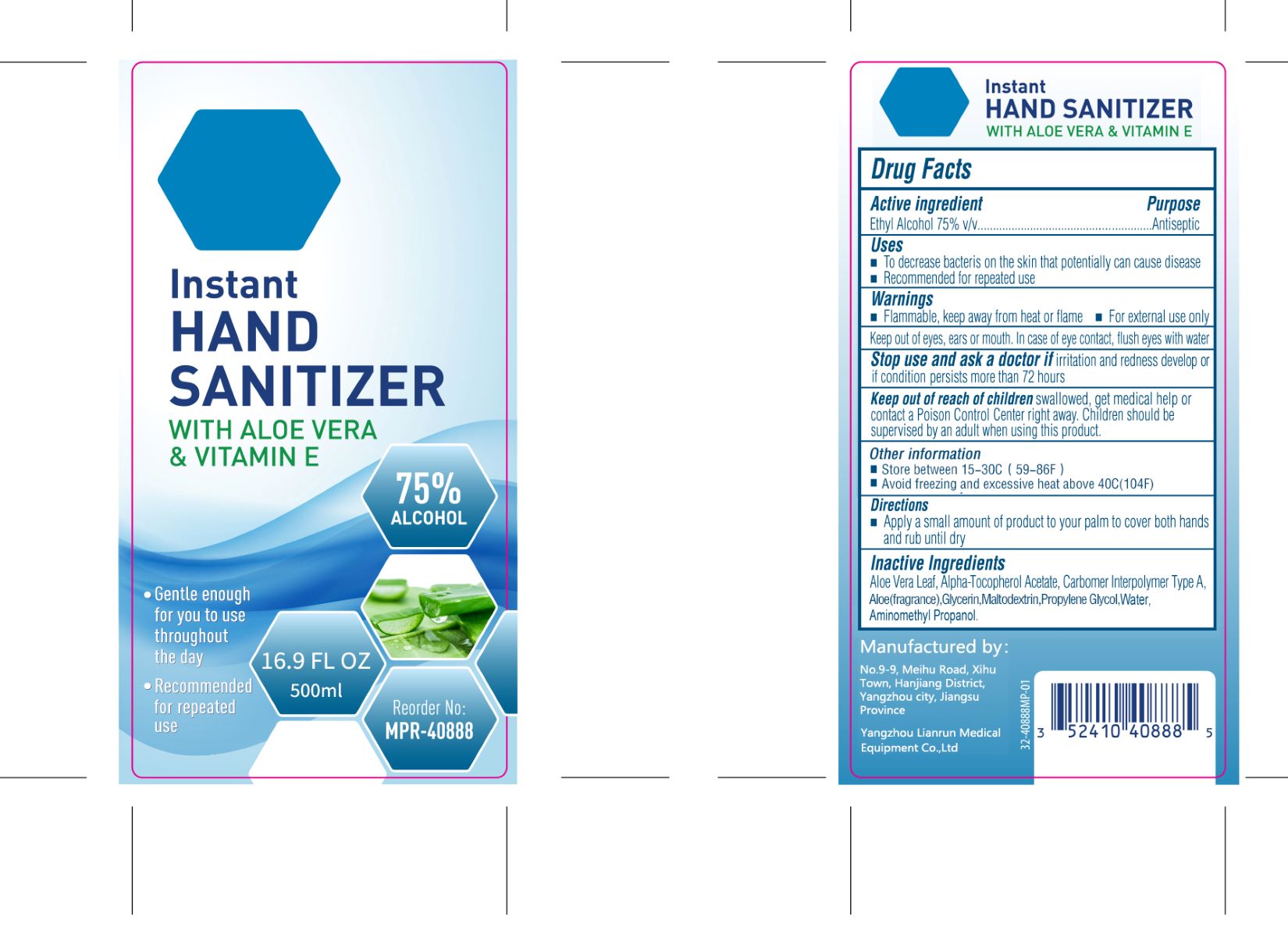 DRUG LABEL: Hand sanitizer
NDC: 93782-002 | Form: GEL
Manufacturer: Yangzhou Lianrun Medical Equipment Co., Ltd.
Category: otc | Type: HUMAN OTC DRUG LABEL
Date: 20201119

ACTIVE INGREDIENTS: ALCOHOL 75 mL/100 mL
INACTIVE INGREDIENTS: ALOE VERA LEAF; PROPYLENE GLYCOL; AMINOMETHYLPROPANOL; CARBOMER COPOLYMER TYPE A; ALOE; .ALPHA.-TOCOPHEROL ACETATE; GLYCERIN; MALTODEXTRIN; WATER

Yangzhou Lianrun Medical Equipment Co., Ltd.
Hand sanitizer
118ml 93782-002-01
500ml 93782-002-02

Active Ingredient(s)

Ethyl Alcohol 75% v/v

Purpose

Antiseptic

Use

- To decrease bacteris on the skin that potentially can cause disease
- Recommended for repeated use

Warnings

- Flammable, keep away from heat or flame
- For external use only
- Keep out of eyes, ears or mouth. In case of eye contact, flush eyes with water

Stop use and ask a doctor if irritation and redness develop or if condition persists more than 72 hours

Keep out of reach of children swallowed, get medical help or contact a Poison Control Center right away. Children should be supervised by an adult when using this product.

Directions

Apply a small amount of product to your palm to cover both hands and rub until dry.

Other information

- Store between 15-30°C(59-86°F)
- Avoid freezing and excessive heat above 40°C(104°F)

Inactive ingredients

Aloe Vera Leaf, Alpha-Tocopherol Acetate, Carbomer Interpolymer Type A, Aloe(fragrance), Glycerin, Maltodextrin, Propylene Glycol, Water, Aminomethyl Propanol.

Package Label - Principal Display Panel

118 mL NDC: 93782-002-01

500 mL NDC: 93782-002-02